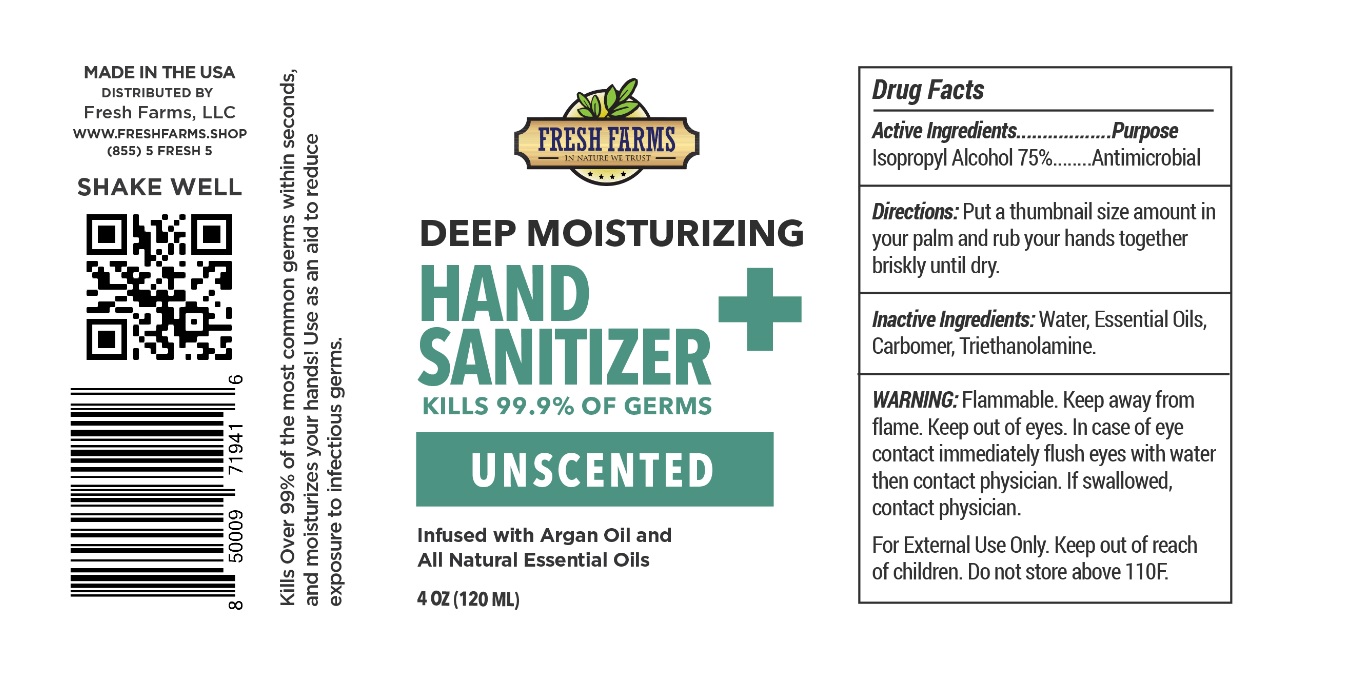 DRUG LABEL: Fresh Farms Deep Moisturizing Hand Sanitizer
NDC: 78215-421 | Form: GEL
Manufacturer: Fresh Farms Llc
Category: otc | Type: HUMAN OTC DRUG LABEL
Date: 20200518

ACTIVE INGREDIENTS: ISOPROPYL ALCOHOL 75 mL/100 mL
INACTIVE INGREDIENTS: CARBOMER HOMOPOLYMER, UNSPECIFIED TYPE; TROLAMINE; TEA TREE OIL; LAVENDER OIL; EUCALYPTUS OIL; GLYCERIN; PROPYLENE GLYCOL; ALOE VERA LEAF; .ALPHA.-TOCOPHEROL; ARGAN OIL

Fresh Farms Hand Sanitizer

Active Ingredients

Isoprpyl Alcohol 75%

Purpose

Antimicrobial

DOSAGE AND ADMINISTRATION

Directions:Put a thumbnail size amount in your palm and rub your hands together briskly until dry.

Inactive Ingredients:Water, Essential Oils, Carbomer, Triethanolamine.

WARNINGS

WARNING: Flammable. Keep away from flame. Keep out of eyes. In case of eye contact immediately flush eyes with water then contact physician. If swallowed, contact physician.

For External Use only. Do not store above 110F.

Keep out of reach of children.

INDICATIONS AND USAGE

Use : to decrease bacteria on the skin that could cause disease.

DEEP MOISTURIZING

KILLS 99.9% OF GERMS

UNSCENTED

Infused with Argan Oil and All Natural Essential Oils

Kills Over 99% of the most common germs within seconds, and moisturizes your hands! Use as an aid to reduce exposure to infectious germs.

MADE IN THE USA

DISTRIBUTED BY

Fresh Farms, LLC

WWW.FRESHFARMS.SHOP

(855) 5 FRESH 5

SHAKE WELL